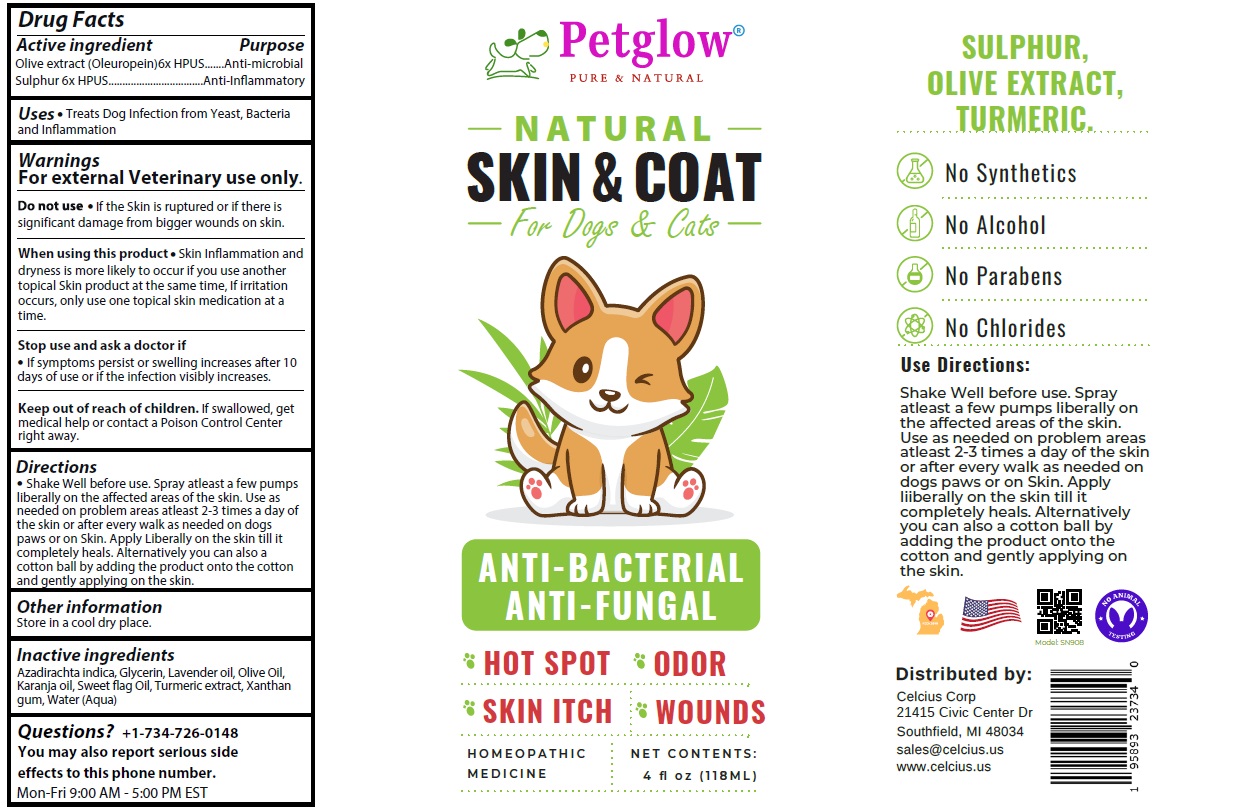 DRUG LABEL: Petglow NATURAL SKIN and COAT
NDC: 83819-090 | Form: SPRAY
Manufacturer: Celcius Corp.
Category: homeopathic | Type: OTC ANIMAL DRUG LABEL
Date: 20260216

ACTIVE INGREDIENTS: OLEA EUROPAEA (OLIVE) LEAF POWDER 6 [hp_X]/118 mL; SULFUR 6 [hp_X]/118 mL
INACTIVE INGREDIENTS: AZADIRACHTA INDICA SEED OIL; GLYCERIN; LAVENDER OIL; OLIVE OIL; KARUM SEED OIL; CALAMUS OIL; TURMERIC; XANTHAN GUM; WATER

Petglow® NATURAL SKIN & COAT

Active ingredient

Olive extract (Oleuropein) 6x HPUS
Sulphur 6x HPUS

Purpose

Anti-microbial
Anti-Inflammatory

Uses

• Treats Dog Infection from Yeast, Bacteria and Inflammation

Warnings

For external Veterinary use only.

Do not use • If the Skin is ruptured or if there is significant damage from bigger wounds on skin.

When using this product • Skin Inflammation and dryness is more likely to occur if you use another topical Skin product at the same time, If irritation occurs, only use one topical skin medication at a time.

Stop use and ask a doctor if
• If symptoms persist or swelling increases after 10 days of use or if the infection visibly increases.

Keep out of reach of children. If swallowed, get medical help or contact a Poison Control Center right away.

Directions

• Shake Well before use. Spray atleast a few pumps liberally on the affected areas of the skin. Use as needed on problem areas atleast 2-3 times a day of the skin or after every walk as needed on dogs paws or on Skin. Apply Liberally on the skin till it completely heals. Alternatively you can also a cotton ball by adding the product onto the cotton and gently applying on the skin.

Other information

Store in a cool dry place.

Inactive ingredients

Azadirachta indica, Glycerin, Lavender oil, Olive Oil, Karanja oil, Sweet flag Oil, Turmeric extract, Xanthan gum, Water (Aqua)

Questions?

+1-734-726-0148
You may also report serious side effects to this phone number.
Mon-Fri 9:00 AM - 5:00 PM EST

PURE & NATURAL

For Dogs & Cats

ANTI-BACTERIAL
ANTI-FUNGAL

HOT SPOT
SKIN ITCH
ODOR
WOUNDS

HOMEOPATHIC MEDICINE

No Synthetics
No Alcohol
No Parabens
No Chlorides

NO ANIMAL TESTING

Distributed by:
Celcius Corp
21415 Civic Center Dr
Southfield, MI 48034
sales@celcius.us
www.celcius.us